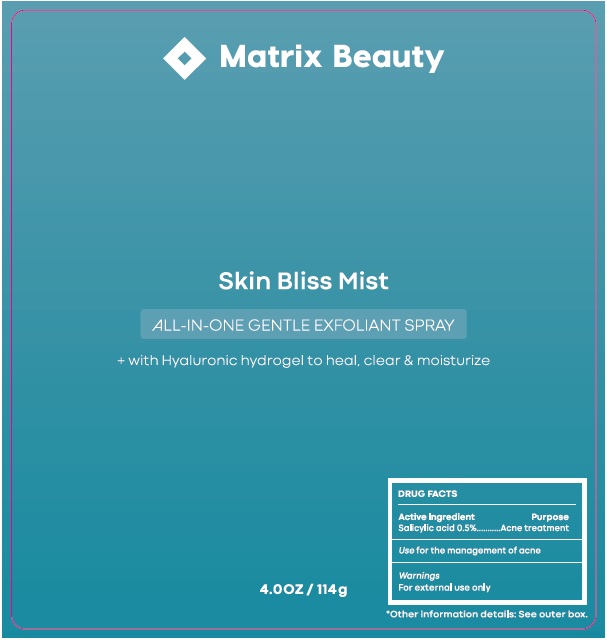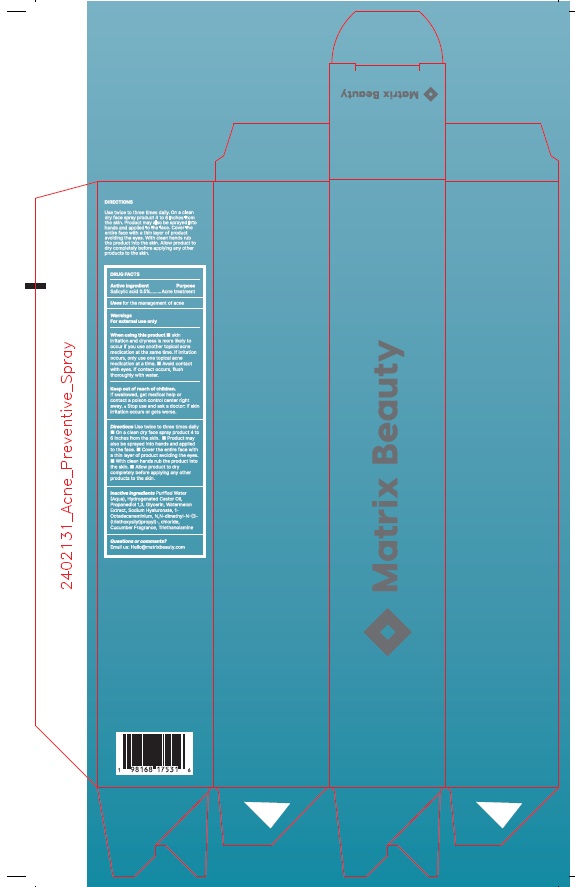 DRUG LABEL: Skin Bliss Mist
NDC: 87156-301 | Form: SPRAY
Manufacturer: Matrix Beauty LLC
Category: otc | Type: HUMAN OTC DRUG LABEL
Date: 20251007

ACTIVE INGREDIENTS: SALICYLIC ACID 0.5 g/100 g
INACTIVE INGREDIENTS: WATER; HYDROGENATED CASTOR OIL; PROPANEDIOL; GLYCERIN; WATERMELON; SODIUM HYALURONATE; TRIETHOXYSILYLPROPYL STEARDIMONIUM CHLORIDE; TRIETHANOLAMINE

Skin Bliss Mist

DRUG FACTS

Active Ingredient:

Salicylic Acid 0.5%

Purpose: Acne Treatment

INDICATIONS AND USAGE

Uses: For the management of acne

Warnings: For external use only

When using this product• Skin irritation and dryness is more likely to occur if you use another topical acne medication at the same time. If irritation occurs, only use one topical acne medication at a time. • Avoid contact with eyes. If contact occurs, flush thoroughly with water.

Keep out of reach of children.

If swallowed, get medical help or contact a poison control center right away. •Stop use and ask a doctor: if skin irritation occurs or gets worse.

DOSAGE AND ADMINISTRATION

Directions Use twice to three times daily • On a clean dry face spray product 4 to 6 inches from skin. • Product may also be sprayed into hands and applied to the face. • Cover the entire face with a thin layer of product avoiding the eyes. • With clean hands rub the product into the skin. • Allow product to dry completely before applying any other products to the skin.

Inactive Ingredients:

Purified Water (Aqua), Hydrogenated Castor Oil, Propanediol 1,3, Glycerin, Watermelon Extract, Sodium Hyaluronate, 1-Octadecanaminium, N,N-dimethyl-N-(3-(triethoxysilyl)propyl)-, chloride, Cucumber Fragrance, Triethanolamine

QUESTIONS

Question or comments?

Email us: Hello@matrixbeauty.com

PACKAGE LABEL

Matrix Beauty

Skin Bliss Mist

ALL-IN-ONE GENTLE EXFOLIANT SPRAY

+ with hyaluronic hydrogel to heal, clear & moisturize

DRUG FACTS

Active ingredient Purpose

Salicylic acid 0.5%................................Acne treatment

Use for the management of acne

Warnings

For external use only

RES